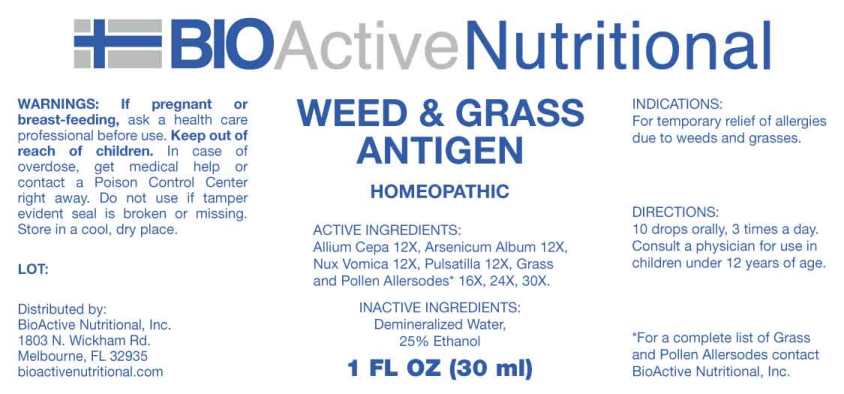 DRUG LABEL: Weed and Grass Antigen
NDC: 43857-0562 | Form: LIQUID
Manufacturer: BioActive Nutritional, Inc.
Category: homeopathic | Type: HUMAN OTC DRUG LABEL
Date: 20230607

ACTIVE INGREDIENTS: ONION 12 [hp_X]/1 mL; ARSENIC TRIOXIDE 12 [hp_X]/1 mL; STRYCHNOS NUX-VOMICA SEED 12 [hp_X]/1 mL; PULSATILLA PRATENSIS WHOLE 12 [hp_X]/1 mL; POA PRATENSIS POLLEN 12 [hp_X]/1 mL; DACTYLIS GLOMERATA TOP 12 [hp_X]/1 mL; CYNODON DACTYLON POLLEN 12 [hp_X]/1 mL; SORGHUM HALEPENSE POLLEN 12 [hp_X]/1 mL; LOLIUM PERENNE POLLEN 12 [hp_X]/1 mL; ANTHOXANTHUM ODORATUM POLLEN 12 [hp_X]/1 mL; PASPALUM NOTATUM POLLEN 12 [hp_X]/1 mL; PHLEUM PRATENSE TOP 12 [hp_X]/1 mL
INACTIVE INGREDIENTS: WATER; ALCOHOL

Drug Facts:

ACTIVE INGREDIENTS:

Allium Cepa, Arsenicum Album, Nux Vomica, Pulsatilla Pratensis, Kentucky Blue Grass, Orchard Grass, Bermuda Grass, Johnson Grass, Rye Grass, Vernal Grass, Bahia Grass, Timothy Grass.

INDICATIONS:

For temporary relief of allergies due to weeds and grasses.

WARNINGS:

If pregnant or breast-feeding, ask a health care professional before use.

Keep out of reach of children. In case of overdose, get medical help or contact a Poison Control Center right away.

Do not use if tamper evident seal is broken or missing.

Store in cool, dry place.

Keep out of reach of children. In case of overdose, get medical help or contact a Poison Control Center right away.

DIRECTIONS:

10 drops orally, 3 times a day. Consult a physician for use in children under 12 years of age.

INDICATIONS:

For temporary relief of allergies due to weeds and grasses.

INACTIVE INGREDIENTS:

Demineralized Water, 25% Ethanol.

QUESTIONS:

Distributed by:

BioActive Nutritional, Inc.

1803 N. Wickham Rd.

Melbourne, FL 32935

bioactivenutritional.com

PACKAGE LABEL DISPLAY:

BIOActive Nutritional

WEED & GRASS

ANTIGEN

HOMEOPATHIC

1 FL OZ (30 ml)